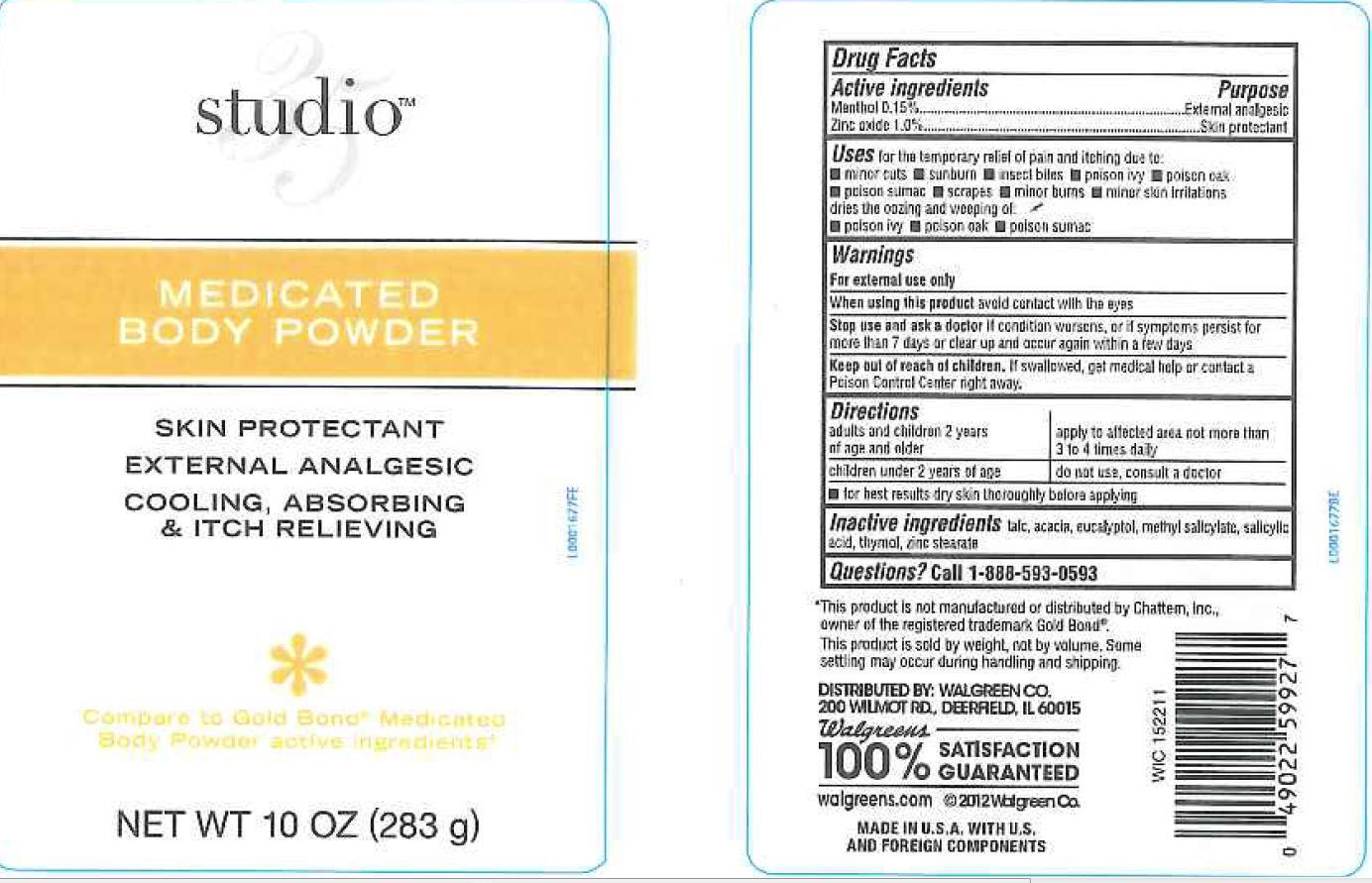 DRUG LABEL: Body
NDC: 0363-0551 | Form: POWDER
Manufacturer: Walgreen Co.
Category: otc | Type: HUMAN OTC DRUG LABEL
Date: 20130318

ACTIVE INGREDIENTS: MENTHOL 1.5 mg/1 g; ZINC OXIDE 10 mg/1 g
INACTIVE INGREDIENTS: TALC; ACACIA; EUCALYPTOL; METHYL SALICYLATE; SALICYLIC ACID; THYMOL; ZINC STEARATE

Drug Facts

Active ingredient

Active ingredients

Menthol 0.15%

Zinc oxide 1.0%

Purpose

External analgesic

Skin protectant

Uses

Uses for temporary relief of pan and itching due to:

- mnor cuts
- sunburn
- insect bites
- poison ivy
- poison oak
- poison sumac
- scrapes
- minor burns
- minor skin irritations

dries the oozing and weeping of:

- poison ivey
- poison oak
- poison sumac

warnings

For external use only

When using this product avoid contact with the eyes

Stop use and ask a doctor if condition worsens, or if symtpoms persist for more than 7 days or clear up and occur again within a few days

Keep out of reach of children. If swallowed, get medical help or contact a Poison Control Center right away.

Directions

adults and children 2 year of age and older - apply to affected area not more than 3 to 4 times daily

children under 2 years of age - do not use, consult a doctor

- for best results dry skin thoroughly before applying

Inactive ingredients

Inactive ingredients talc, acacia, eucaluptol, methyl salicylate, salicylic acid, thymol, zinc stearate

Questions

Questions? Call 1-888-593-0593

Disclaimer

Ths product is not manufacgtured or distributed by Chattem, Inc., owener of the registered tradmark of Gold Bond

This produc is sold by weight, not by volume. Some settling may occur during handling and shipping

Adverse reactins

DISTRIBUTED BY: WALGREEN CO.

200 WILMOT RD, DEERFIELD, IL 60015

100% SATISFACTIN GUARANTEED

walgreens.com

MADE IN U.S.A. WITH U.S. AND FOREIGN COMPONENTS

Principal Display Panel

Studio 35

MEDICATED

BODY POWDER

SKIN PROTECTANT

EXTERNAL ANALGESIC

COOLING, ABSORBING

+ ITCH RELIEVING

Compare to Gold Bond Medicated Body Powder active ingredient

NET T 10 OZ (283 g)